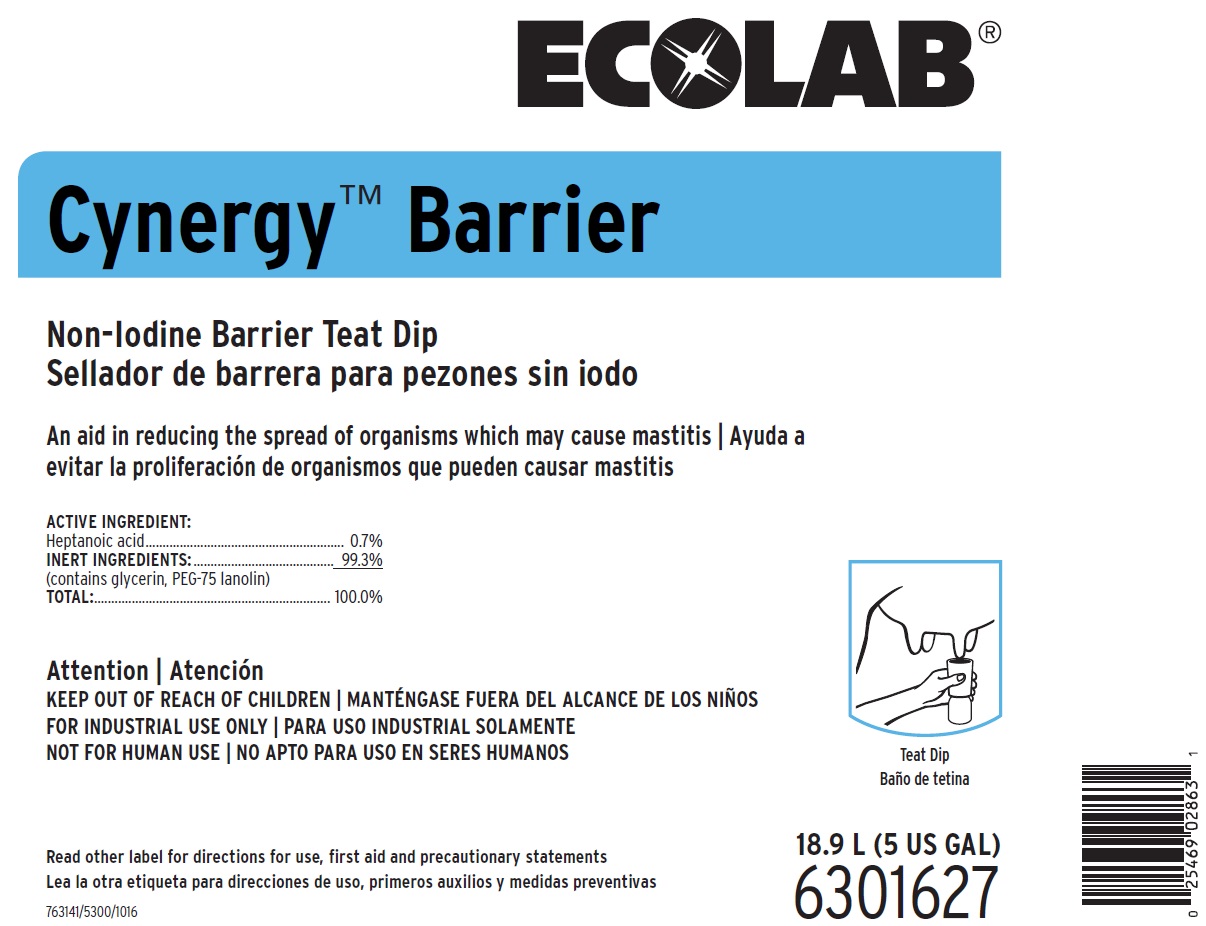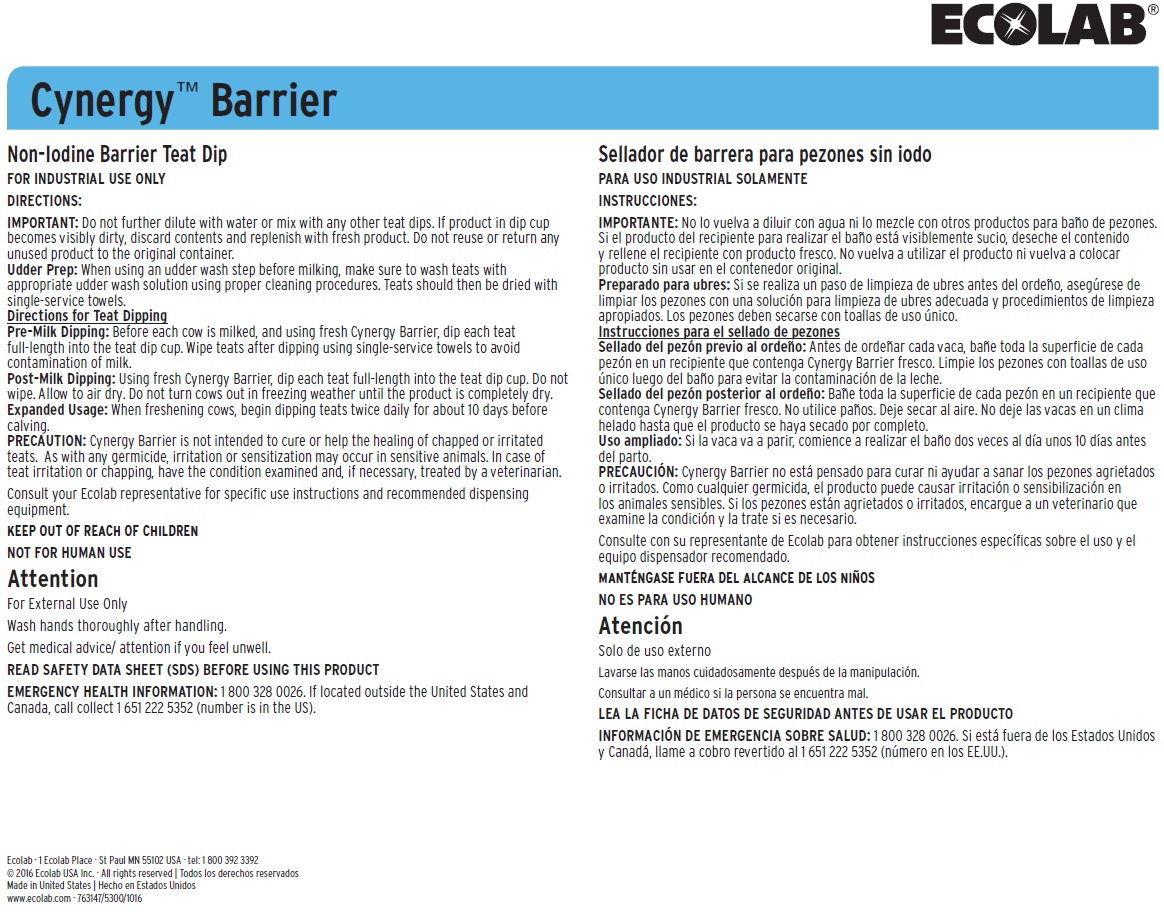 DRUG LABEL: Cynergy Barrier
NDC: 47593-445 | Form: SOLUTION
Manufacturer: Ecolab Inc
Category: animal | Type: OTC ANIMAL DRUG LABEL
Date: 20251012

ACTIVE INGREDIENTS: HEPTANOIC ACID 7 mg/1 mL
INACTIVE INGREDIENTS: WATER; GLYCERIN; PEG-75 LANOLIN

SAFE HANDLING WARNING

Attention

For External Use Only

Wash hands thoroughly after handling.

Get medical advice/ attention if you feel unwell.

KEEP OUT OF REACH OF CHILDREN

FOR INDUSTRIAL USE ONLY

NOT FOR HUMAN USE

Read other label for directions for use, first aid and precautionary statements

DIRECTIONS:

IMPORTANT: Do not further dilute with water or mix with any other teat dips. If product in dip cup becomes visibly dirty, discard contents and replenish with fresh product. Do not reuse or return any unused product to the original container.

Udder Prep: When using an udder wash step before milking, make sure to wash teats with appropriate udder wash solution using proper cleaning procedures. Teats should then be dried with single-service towels.

Directions for Teat Dipping

Pre-Milk Dipping: Before each cow is milked, and using fresh Cynergy Barrier, dip each teat full-length into the teat dip cup. Wipe teats after dipping using single-service towels to avoid contamination of milk.

Post-Milk Dipping: Using fresh Cynergy Barrier, dip each teat full-length into the teat dip cup. Do not wipe. Allow to air dry. Do not turn cows out in freezing weather until the product is completely dry. Expanded Usage: When freshening cows, begin dipping teats twice daily for about 10 days before calving.

PRECAUTION: Cynergy Barrier is not intended to cure or help the healing of chapped or irritated teats. As with any germicide, irritation or sensitization may occur in sensitive animals. In case of teat irritation or chapping, have the condition examined and, if necessary, treated by a veterinarian.

Consult your Ecolab representative for specific use instructions and recommended dispensing equipment.

OTHER SAFETY INFORMATION

For External Use Only

Wash hands thoroughly after handling.

Get medical advice/ attention if you feel unwell.

READ SAFETY DATA SHEET (SDS) BEFORE USING THIS PRODUCT

EMERGENCY HEALTH INFORMATION: 1 800 328 0026. If located outside the United States and

Canada, call collect 1 651 222 5352 (number is in the US).

PACKAGE LABEL

ECOLAB®

CYNERGY™ BARRIER

Non-Iodine Barrier Teat Dip

An Aid in Reducing the Spread of Organisms Which May Cause Mastitis

ACTIVE INGREDIENT:

Heptanoic acid...................................................0.7%

INERT INGREDIENTS: ........................................99.3%

(contains glycerin, PEG-75 lanolin)

TOTAL:.............................................................100.0%

18.9 L (5 US GAL)